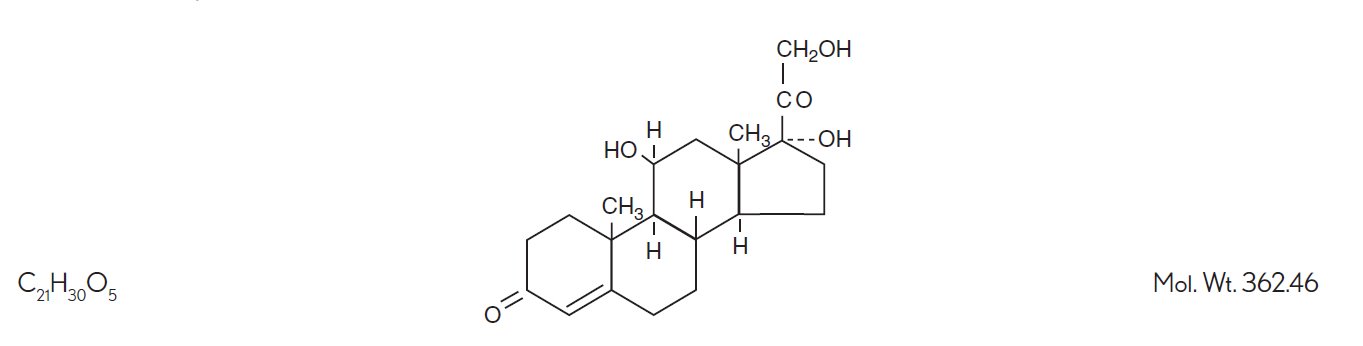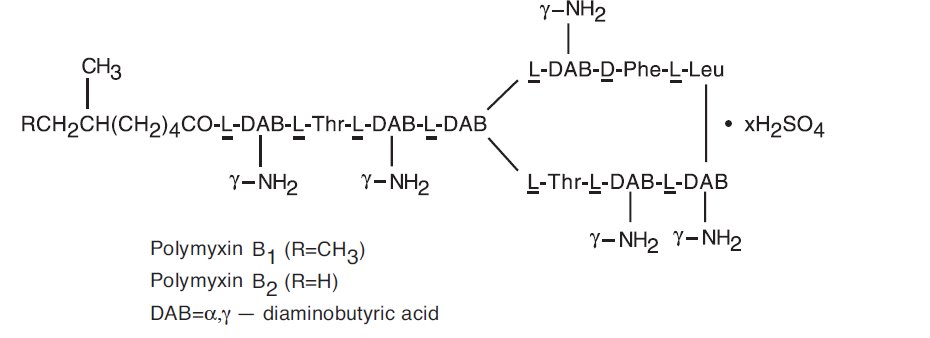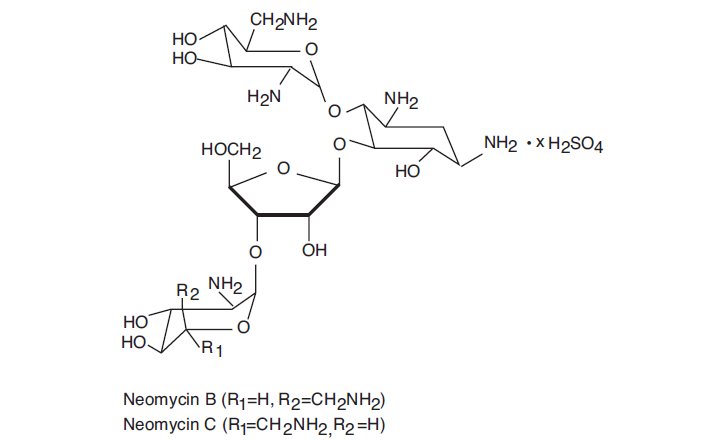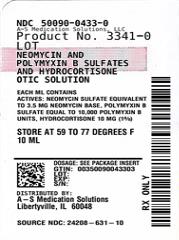 DRUG LABEL: Neomycin and Polymyxin B Sulfates and Hydrocortisone
NDC: 50090-0433 | Form: SOLUTION/ DROPS
Manufacturer: A-S Medication Solutions
Category: prescription | Type: HUMAN PRESCRIPTION DRUG LABEL
Date: 20260204

ACTIVE INGREDIENTS: NEOMYCIN SULFATE 3.5 mg/1 mL; POLYMYXIN B SULFATE 10000 [USP'U]/1 mL; HYDROCORTISONE 10 mg/1 mL
INACTIVE INGREDIENTS: PROPYLENE GLYCOL; HYDROCHLORIC ACID; POTASSIUM METABISULFITE; CUPRIC SULFATE; GLYCERIN; AQUA

Neomycin and Polymyxin B Sulfates
and Hydrocortisone Otic Solution, USP
(Sterile)

DESCRIPTION

Neomycin and polymyxin B sulfates and hydrocortisone otic solution, USP is a sterile antibacterial and anti-inflammatory solution for otic use.

Each mL contains: Actives:neomycin sulfate equivalent to 3.5 mg neomycin base, polymyxin B sulfate equivalent to 10,000 polymyxin B units, and hydrocortisone 10 mg (1%); Inactives:propylene glycol, hydrochloric acid, potassium metabisulfite, cupric sulfate, glycerin, purified water. The pH range is 2.0 to 4.5.

Neomycin sulfate is the sulfate salt of neomycin B and C, which are produced by the growth of Streptomyces fradiaeWaksman (Fam. Streptomycetaceae). It has a potency equivalent of not less than 600 mcg of neomycin standard per mg, calculated on an anhydrous basis. The structural formulae are:

Polymyxin B sulfate is the sulfate salt of polymyxin B1and B2, which are produced by the growth of Bacillus polymyxa,(Prazmowski) Migula (Fam. Bacillaceae). It has a potency of not less than 6,000 polymyxin B units per mg, calculated on an anhydrous basis. The structural formulae are:

Hydrocortisone, 11β, 17, 21 - trihydroxypregn-4-ene-3, 20-dione, is an anti-inflammatory hormone. Its structural formula is:

CLINICAL PHARMACOLOGY

Corticoids suppress the inflammatory response to a variety of agents and they may delay healing. Since corticoids may inhibit the body's defense mechanism against infection, a concomitant antimicrobial drug may be used when this inhibition is considered to be clinically significant in a particular case.

The anti-infective components in the combination are included to provide action against specific organisms susceptible to them. Neomycin sulfate and polymyxin B sulfate together are considered active against the following microorganisms: Staphylococcus aureus, Escherichia coli, Haemophilus influenzae, Klebsiella-Enterobacterspecies, Neisseriaspecies, and Pseudomonas aeruginosa.This product does not provide adequate coverage against Serratia marcescensand streptococci, including Streptococcus pneumoniae.

The relative potency of corticosteroids depends on the molecular structure, concentration, and release from the vehicle.

INDICATIONS AND USAGE

For the treatment of superficial bacterial infections of the external auditory canal caused by organisms susceptible to the action of the antibiotics.

CONTRAINDICATIONS

This product is contraindicated in those individuals who have shown hypersensitivity to any of its components. This product should not be used if the external auditory canal disorder is suspected or known to be due to cutaneous viral infection (for example, herpes simplex virus or varicella zoster virus).

WARNINGS

Neomycin can induce permanent sensorineural hearing loss due to cochlear damage, mainly destruction of hair cells in the organ of Corti. The risk of ototoxicity is greater with prolonged use; therefore, duration of therapy should be limited to 10 consecutive days (see PRECAUTIONS - General).

Patients being treated with eardrops containing neomycin should be under close clinical observation. Due to its acidity, which may cause burning and stinging, neomycin and polymyxin B sulfates and hydrocortisone otic solution should not be used in any patients with a perforated tympanic membrane.

Neomycin sulfate may cause cutaneous sensitization. A precise incidence of hypersensitivity reactions (primarily skin rash) due to topical neomycin is not known. Discontinue this product promptly if sensitization or irritation occurs.

When using neomycin-containing products to control secondary infection in the chronic dermatoses, such as chronic otitis externa or stasis dermatitis, it should be borne in mind that the skin in these conditions is more liable than is normal skin to become sensitized to many substances, including neomycin. The manifestation of sensitization to neomycin is usually a low-grade reddening with swelling, dry scaling, and itching; it may be manifested simply as a failure to heal. Periodic examination for such signs is advisable, and the patient should be told to discontinue the product if they are observed. These symptoms regress quickly on withdrawing the medication. Neomycin-containing applications should be avoided for the patient thereafter.

Contains potassium metabisulfite, a sulfite that may cause allergic-type reactions including anaphylactic symptoms and life-threatening or less severe asthmatic episodes in certain susceptible people. The overall prevalence of sulfite sensitivity in the general population is unknown and probably low. Sulfite sensitivity is seen more frequently in asthmatic than in nonasthmatic people.

PRECAUTIONS

General

As with other antibiotic preparations, prolonged use may result in overgrowth of nonsusceptible organisms, including fungi.

If the infection is not improved after 1 week, cultures and susceptibility tests should be repeated to verify the identity of the organism and to determine whether therapy should be changed.

Treatment should not be continued for longer than 10 days.

Allergic cross-reactions may occur which could prevent the use of any or all of the following antibiotics for the treatment of future infections: kanamycin, paromomycin, streptomycin, and possibly, gentamicin.

Information for Patients

Avoid contaminating bottle tip with material from the ear, fingers or other source. This caution is necessary if the sterility of the drops is to be preserved.

If sensitization or irritation occurs, discontinue use immediately and contact your physician.

Do not use in the eyes.

Laboratory Tests

Systemic effects of excessive levels of hydrocortisone may include a reduction in the number of circulating eosinophils and a decrease in urinary excretion of 17-hydroxycorticosteroids.

Carcinogenesis, Mutagenesis, Impairment of Fertility

Long-term studies in animals (rats, rabbits, mice) showed no evidence of carcinogenicity attributable to oral administration of corticosteroids.

Pregnancy

Teratogenic Effects

Corticosteroids have been shown to be teratogenic in rabbits when applied topically at concentrations of 0.5% on days 6 to 18 of gestation and in mice when applied topically at a concentration of 15% on days 10 to 13 of gestation. There are no adequate and well-controlled studies in pregnant women. Corticosteroids should be used during pregnancy only if the potential benefit justifies the potential risk to the fetus.

Nursing Mothers

Hydrocortisone appears in human milk following oral administration of the drug. Since systemic absorption of hydrocortisone may occur when applied topically, caution should be exercised when neomycin and polymyxin B sulfates and hydrocortisone otic solution is used by a nursing woman.

Pediatric Use

The safety and effectiveness of neomycin and polymyxin B sulfates and hydrocortisone otic solution in otitis externa have been established in the pediatric age group 2 years to 16 years of age. There is inadequate data to establish safety and effectiveness in otitis externa for pediatric patients under 2 years of age.^1

Geriatric Use

Clinical studies of neomycin and polymyxin B sulfates and hydrocortisone otic solution did not include sufficient numbers of subjects aged 65 and over to determine whether they respond differently from younger subjects. Other reported clinical experience has not identified differences in responses between the elderly and younger patients.

ADVERSE REACTIONS

Neomycin occasionally causes skin sensitization. Ototoxicity and nephrotoxicity have also been reported (see WARNINGS). Adverse reactions have occurred with topical use of antibiotic combinations including neomycin and polymyxin B. Exact incidence figures are not available since no denominator of treated patients is available. The reaction occurring most often is allergic sensitization. In one clinical study, using a 20% neomycin patch, neomycin-induced allergic skin reactions occurred in two of 2,175 (0.09%) individuals in the general population.^2In another study, the incidence was found to be approximately 1%.^3

Skin hyperpigmentation has been reported with polymyxin B containing products.

The following local adverse reactions have been reported with topical corticosteroids, especially under occlusive dressings: burning, itching, irritation, dryness, folliculitis, hypertrichosis, acneiform eruptions, hypopigmentation, perioral dermatitis, allergic contact dermatitis, maceration of the skin, secondary infection, skin atrophy, striae, and miliaria. Stinging and burning have been reported when this product has gained access to the middle ear.

To report SUSPECTED ADVERSE REACTIONS, contact Bausch & Lomb Incorporated at 1-800-553-5340 or FDA at 1-800-FDA-1088 or www.fda.gov/medwatch.

DOSAGE AND ADMINISTRATION

Therapy with this product should be limited to 10 consecutive days. The external auditory canal should be thoroughly cleansed and dried with a sterile cotton applicator.

For adults, four drops of the solution should be instilled into the affected ear 3 or 4 times daily. For infants and children, three drops are suggested because of the smaller capacity of the ear canal.

The patient should lie with the affected ear upward and then the drops should be instilled. This position should be maintained for 5 minutes to facilitate penetration of the drops into the ear canal.

Repeat, if necessary, for the opposite ear.

If preferred, a cotton wick may be inserted into the canal and then the cotton may be saturated with the solution. This wick should be kept moist by adding further solution every 4 hours. The wick should be replaced at least once every 24 hours.

HOW SUPPLIED

Product: 50090-0433

NDC: 50090-0433-0 10 mL in a BOTTLE, DROPPER / 1 in a CARTON

REFERENCES

1. Jones RN, Milazzo J, Seidlin M. Ofloxacin Otic Solution for Treatment of Otitis Externa in Children and Adults. Arch Otolaryngol Head Neck Surg. 1997; 123:1193-1200.

2. Leyden JJ, Kligman AM. Contact dermatitis to neomycin sulfate. JAMA. 1979; 242:1276-1278.

3. Prystowsky SD, Allen AM, Smith RW, Nonomura JH, Odom RB, Akers WA. Allergic contact hypersensitivity to nickel, neomycin, ethylenediamine, and benzocaine: relationships between age, sex, history of exposure, and reactivity to standard patch tests and use tests in a general population. Arch Dermatol. 1979; 115:959-962.

Distributed by:

Bausch & Lomb Americas Inc.

Bridgewater, NJ 08807 USA

Manufactured by:

Bausch & Lomb Incorporated

Tampa, FL 33637 USA

© 2025 Bausch & Lomb Incorporated or its affiliates

Revised: September 2025

9072108 (Folded)

9072208 (Flat)